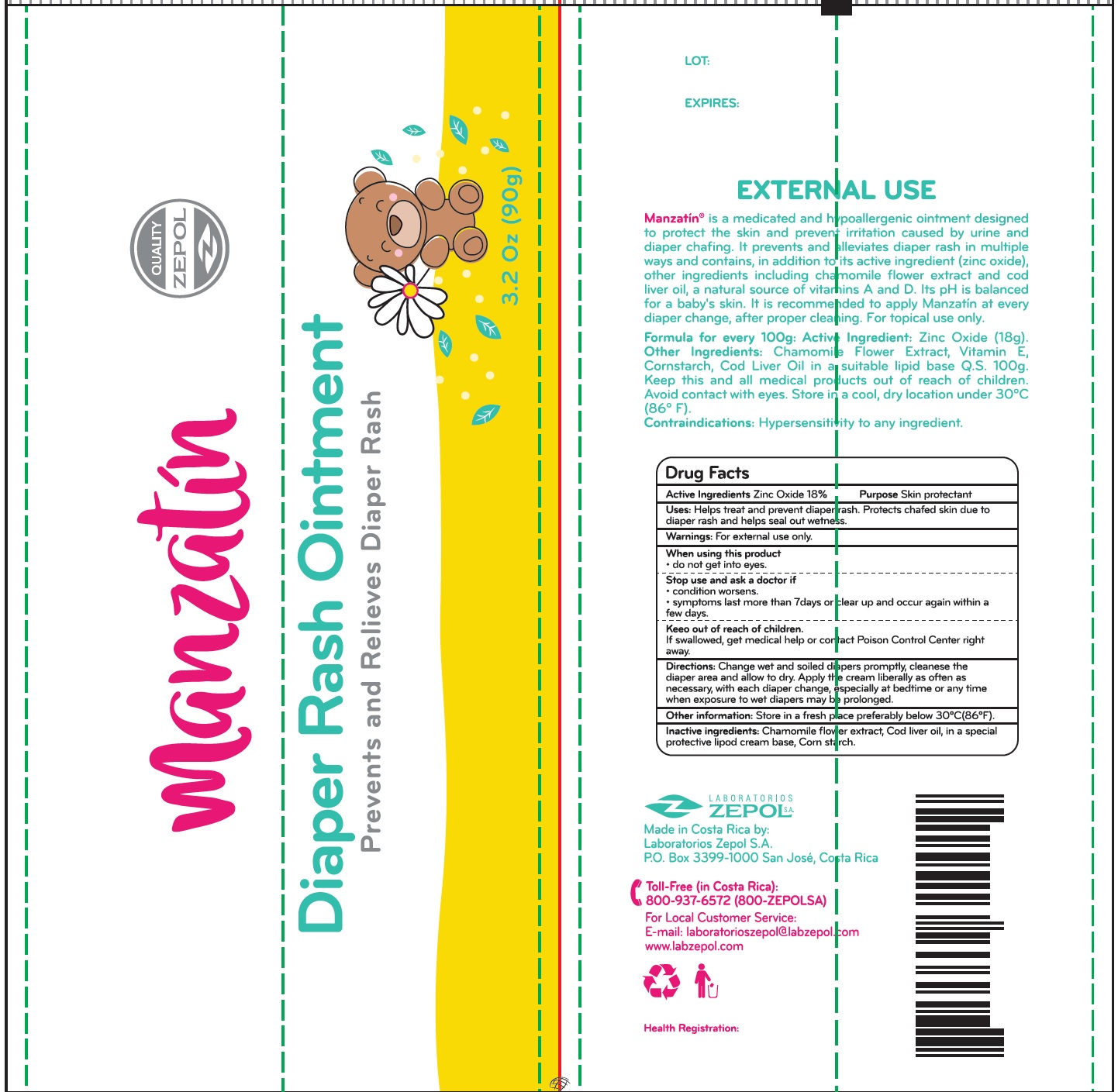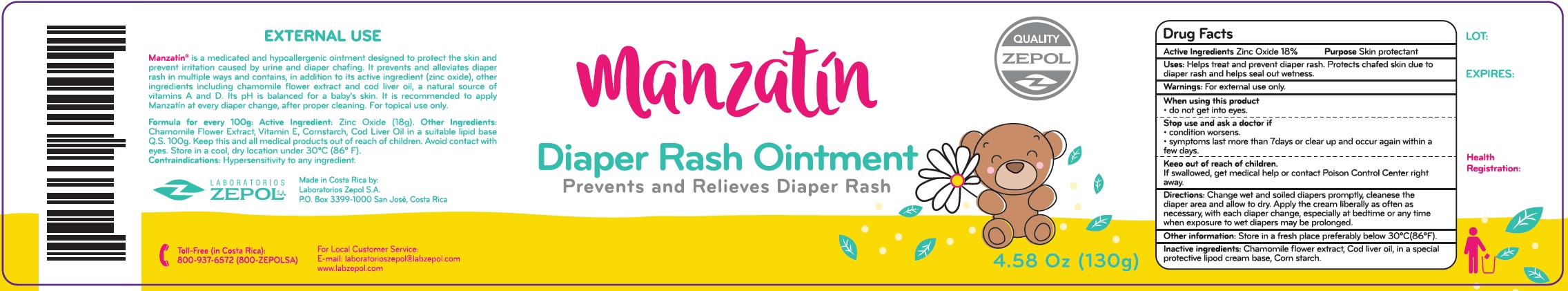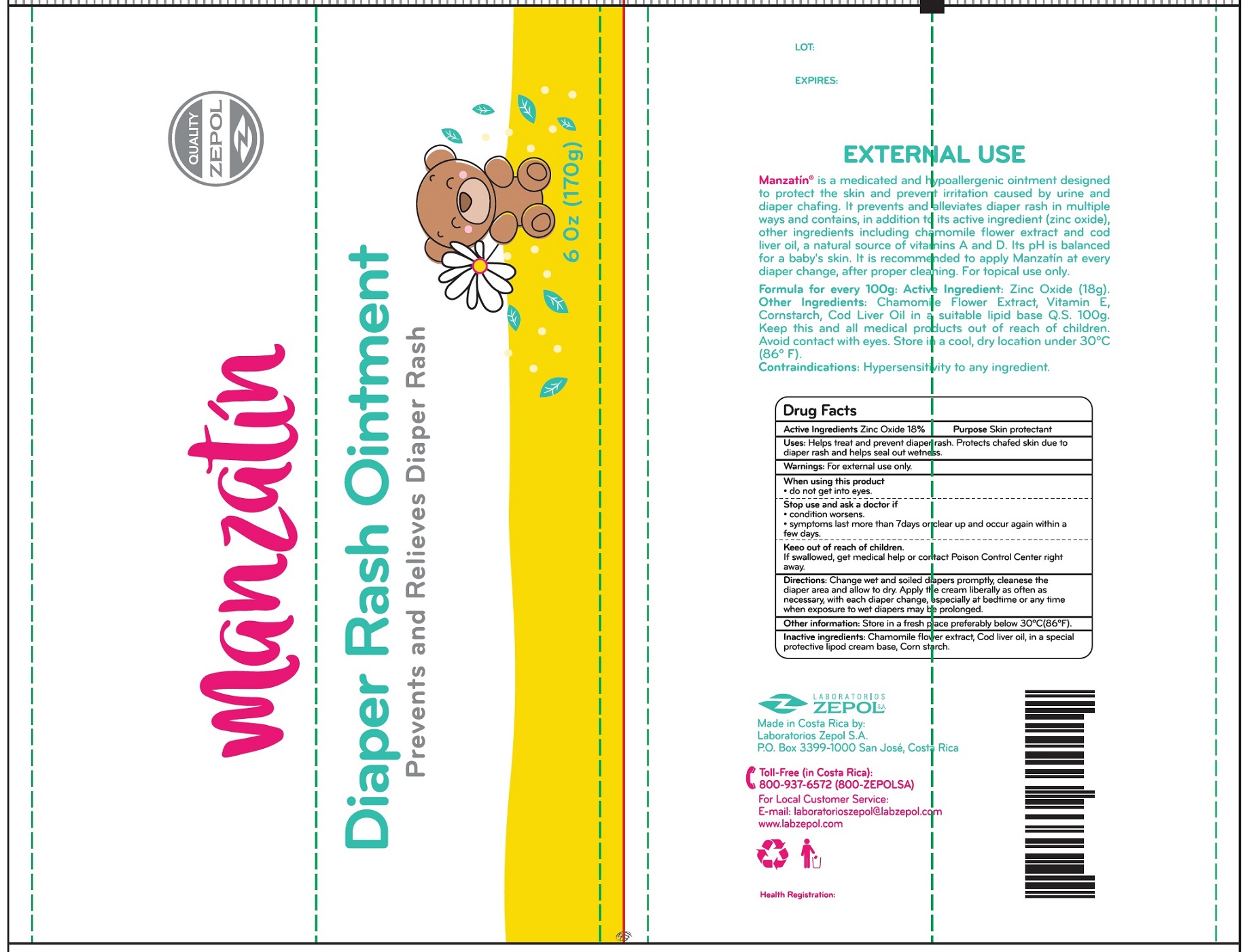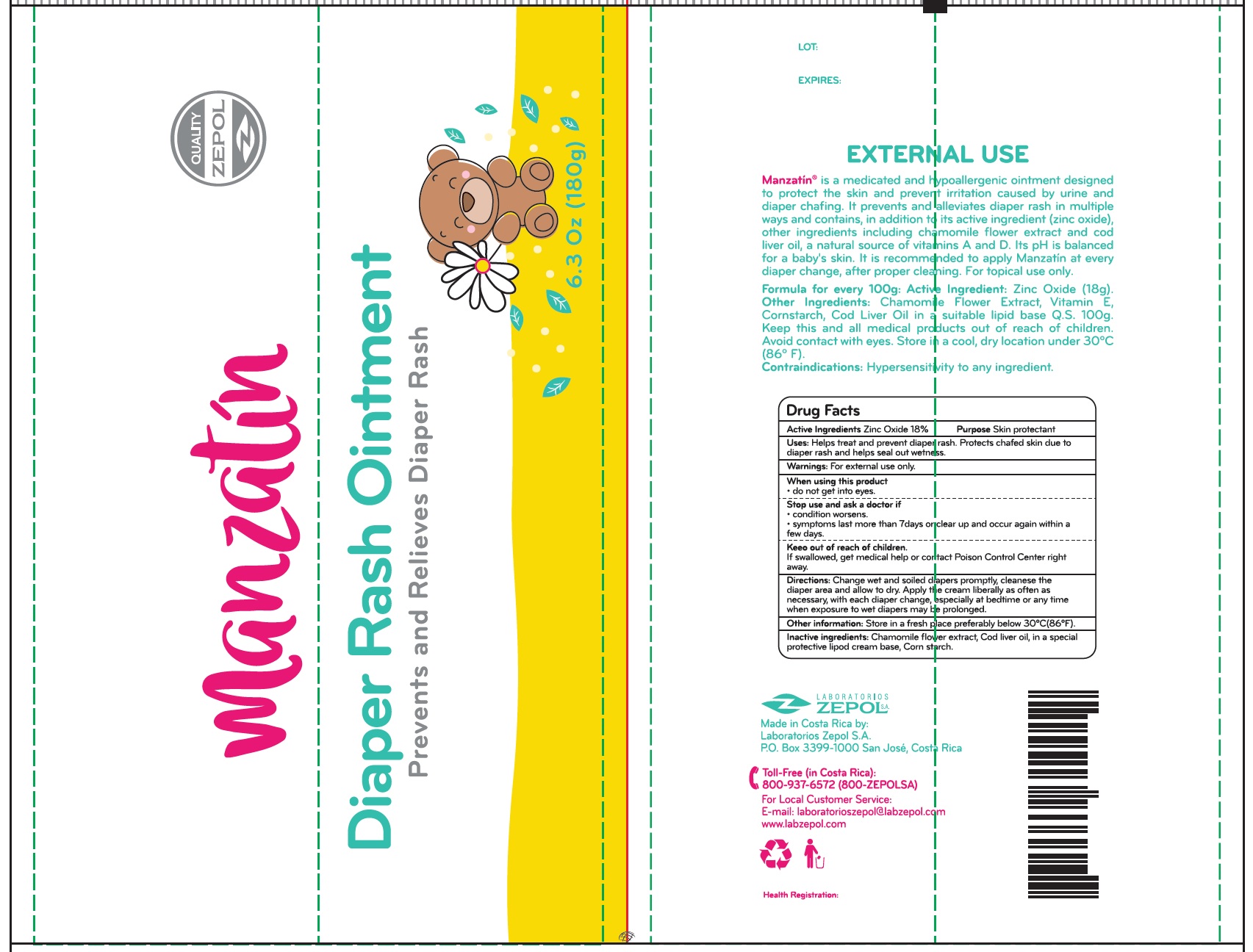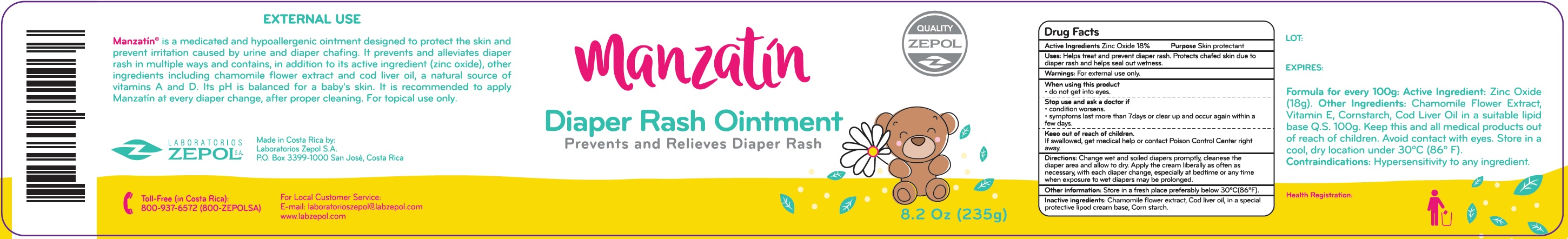 DRUG LABEL: Manzatin Diaper Rash Skin Protectant
NDC: 55715-005 | Form: OINTMENT
Manufacturer: Laboratorios Zepol S.A.
Category: otc | Type: HUMAN OTC DRUG LABEL
Date: 20231201

ACTIVE INGREDIENTS: ZINC OXIDE 180 mg/1 g
INACTIVE INGREDIENTS: CHAMAEMELUM NOBILE FLOWER; COD LIVER OIL; STARCH, CORN

Manzatin Diaper Rash Skin Protectant

Active Ingredients

Zinc Oxide 18%

Purpose

Skin protectant

Uses:

Helps treat and prevent diaperash. Protects chafed skin due to diaper rash and helps seal out wetness.

Warnings:

For external use only.

When using this product

- do not get into eyes.

Stop use and ask a doctor if

- condition worsens.
- symptoms last more than 7days or clear up and occur again within a few days.

Keep out of reach of children.

If swallowed, get mediccal help or contact Poison Control Center right away.

Directions:

Change wet and soiled diapers promptly, cleanese the diaper area and allow to dry. Apply the cream liberally as often as necessary, with each diaper change, especially at bedtime or any time when exposure to wet diapers may be prolonged.

Other infomation:

Store in a fresh place preferably below 30°C(86°F).

Inactive ingredients:

Chamomile flower extract, Cod liver oil, in special protective lipod cream base, Corn starch.